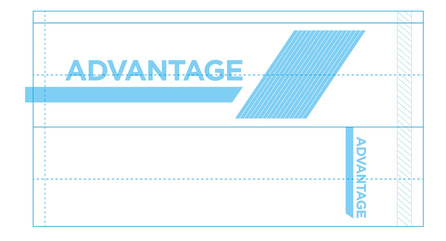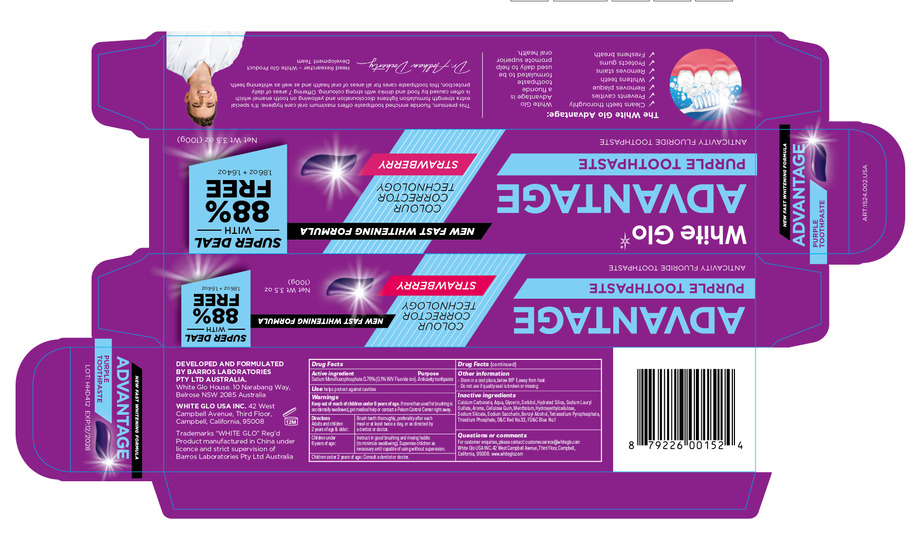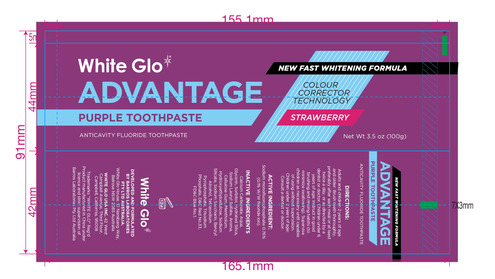 DRUG LABEL: purple tooth
NDC: 82168-005 | Form: PASTE
Manufacturer: Guangzhou City Caiye Cosmetics CO., Ltd
Category: otc | Type: HUMAN OTC DRUG LABEL
Date: 20241212

ACTIVE INGREDIENTS: SODIUM MONOFLUOROPHOSPHATE 0.76 g/100 g
INACTIVE INGREDIENTS: CALCIUM CARBONATE; WATER; GLYCERIN; SORBITOL; SILICA; SODIUM LAURYL SULFATE; CELLULOSE GUM; SODIUM SILICATE; BENZYL ALCOHOL; TETRASODIUM PYROPHOSPHATE; HYDROXYETHYLCELLULOSE; MENTHOL; SODIUM SACCHARIN

82168-005

Active Ingredient(s)

Sodium monofluorophosphate 0.76%

Purpose

Anticavity tothpaste

Use

Use helps protect against cavities

Warnings

Keep out of reach of children under 6 years of age. If more than used for brushing is
acidentally sallowed, get medical help or contact a Poison Control Center right away.

Do not use on open skin wounds

WHEN USING

Please keep away from your eyes when using this product

STOP USE

If in contact with the eyes, rinse thoroughly with water.

Keep out of reach of children under 6 years of age.

Directions

Adults and children 2 years of age & older: Brush teth thoroughly, preferably after each meal or at least twice a day, or as directed by
a dentist or doctor.
Children under 6 years of age: Instruct in good brushing and rinsing habits (to minimize swallowing). Supervise children as necessary

until capable of using without supervision,

Children under 2 years of age: Consult a dentist or doctor.

Other information

Store in a cool place below 86° F away from heat
Do not use if quality seal is broken or missing

Inactive ingredients

Calcium Carbonate, Aqua (Water), Glycerin, Sorbito, Slica, Aroma (Flavour), Sodium Lauryl Sulphate,

Copernicia Cerifera (Carnauba) Wax, Carboxymethyl Hyoroyetlhl-llulose, Chondrus Crispus (arrageenan),

Sodium Saccharin, Rosa Canina Fruit 0i, CI 77891